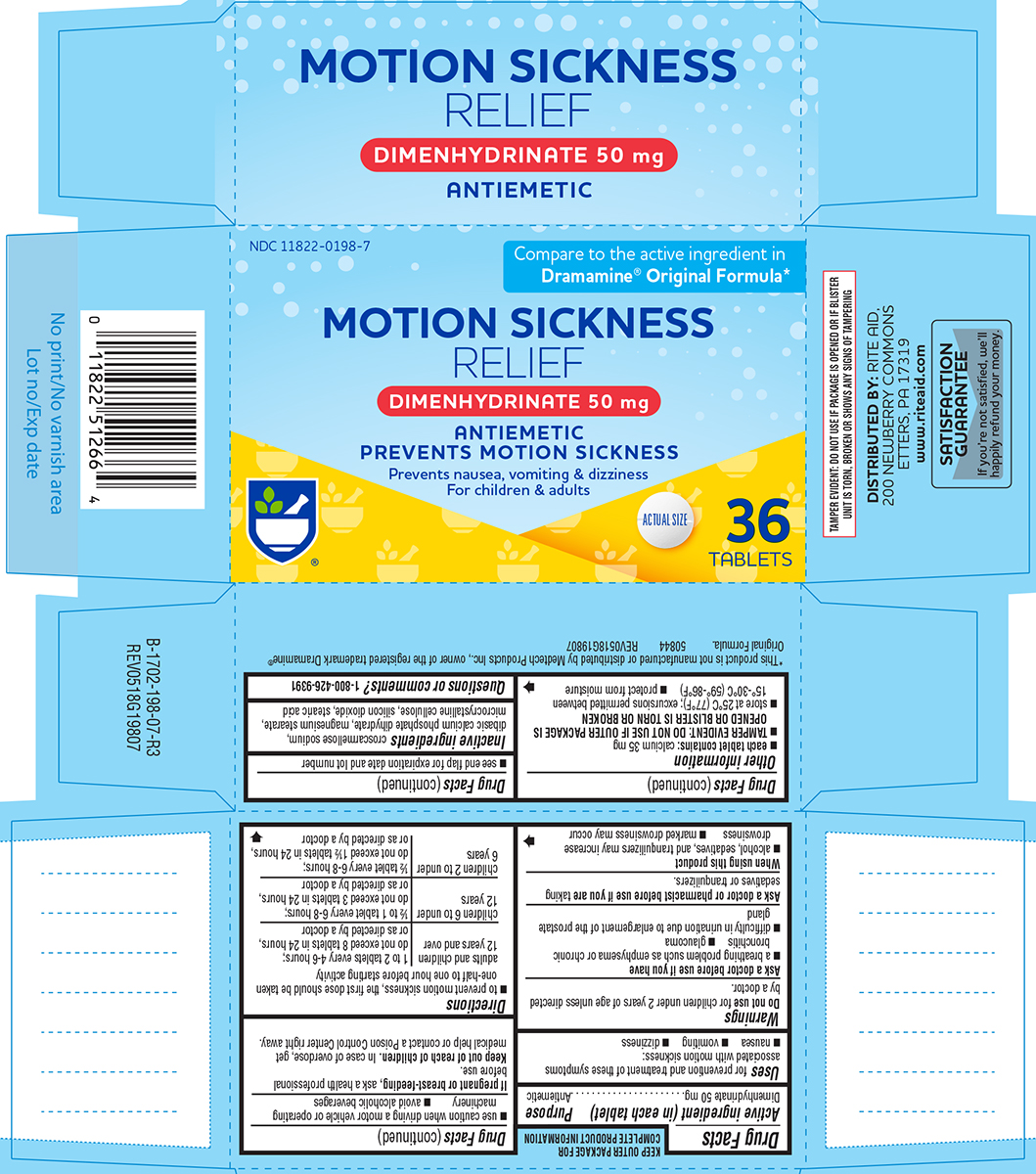 DRUG LABEL: Motion Sickness Relief
NDC: 11822-0198 | Form: TABLET
Manufacturer: Rite Aid Corporation
Category: otc | Type: HUMAN OTC DRUG LABEL
Date: 20260107

ACTIVE INGREDIENTS: DIMENHYDRINATE 50 mg/1 1
INACTIVE INGREDIENTS: CROSCARMELLOSE SODIUM; DIBASIC CALCIUM PHOSPHATE DIHYDRATE; MAGNESIUM STEARATE; MICROCRYSTALLINE CELLULOSE; SILICON DIOXIDE; STEARIC ACID

Rite Aid 44-198

Active ingredient (in each tablet)

Dimenhydrinate 50 mg

Purpose

Antiemetic

Uses

for prevention and treatment of these symptoms associated with motion sickness:

- nausea
- vomiting
- dizziness

Warnings

Do not use

for children under 2 years of age unless directed by a doctor.

Ask a doctor before use if you have

- a breathing problem such as emphysema or chronic bronchitis
- glaucoma
- difficulty in urination due to enlargement of the prostate gland

Ask a doctor or pharmacist before use if you are

taking sedatives or tranquilizers.

When using this product

- alcohol, sedatives, and tranquilizers may increase drowsiness
- marked drowsiness may occur
- use caution when driving a motor vehicle or operating machinery
- avoid alcoholic beverages

If pregnant or breast-feeding,

ask a health professional before use.

Keep out of reach of children.

In case of overdose, get medical help or contact a Poison Control Center right away.

Directions

- to prevent motion sickness, the first dose should be taken one-half to one hour before starting activity

adults and children 12 years and over | 1 to 2 tablets every 4-6 hours; do not exceed 8 tablets in 24 hours, or as directed by a doctor
children 6 to under 12 years | ½ to 1 tablet every 6-8 hours; do not exceed 3 tablets in 24 hours, or as directed by a doctor
children 2 to under 6 years | ½ tablet every 6-8 hours; do not exceed 1½ tablets in 24 hours, or as directed by a doctor

Other information

- each tablet contains: calcium 35 mg
- TAMPER EVIDENT: DO NOT USE IF OUTER PACKAGE IS OPENED OR BLISTER IS TORN OR BROKEN
- store at 25ºC (77ºF); excursions permitted between 15º-30ºC (59º-86ºF)
- protect from moisture
- see end flap for expiration date and lot number

Inactive ingredients

croscarmellose sodium, dibasic calcium phosphate dihydrate, magnesium stearate, microcrystalline cellulose, silicon dioxide, stearic acid

Questions or comments?

1-800-426-9391

Principal Display Panel

NDC 11822-0198-7

Compare to the active ingredient in
Dramamine® Original Formula*

MOTION SICKNESS
RELIEF
DIMENHYDRINATE 50 mg

ANTIEMETIC
PREVENTS MOTION SICKNESS

Prevents nausea, vomiting & dizziness
For children & adults

ACTUAL SIZE

36 TABLETS

TAMPER EVIDENT: DO NOT USE IF PACKAGE IS OPENED OR IF BLISTER
UNIT IS TORN, BROKEN OR SHOWS ANY SIGNS OF TAMPERING

* This product is not manufactured or distributed by Medtech Products Inc., owner of the registered trademark Dramamine®
Original Formula. 50844 REV0518G19807

DISTRIBUTED BY: RITE AID,
200 NEWBERRY COMMONS
ETTERS, PA 17319
www.riteaid.com

SATISFACTION
GUARANTEE
If you're not satisfied, we'll
happily refund your money.

Rite Aid 44-198